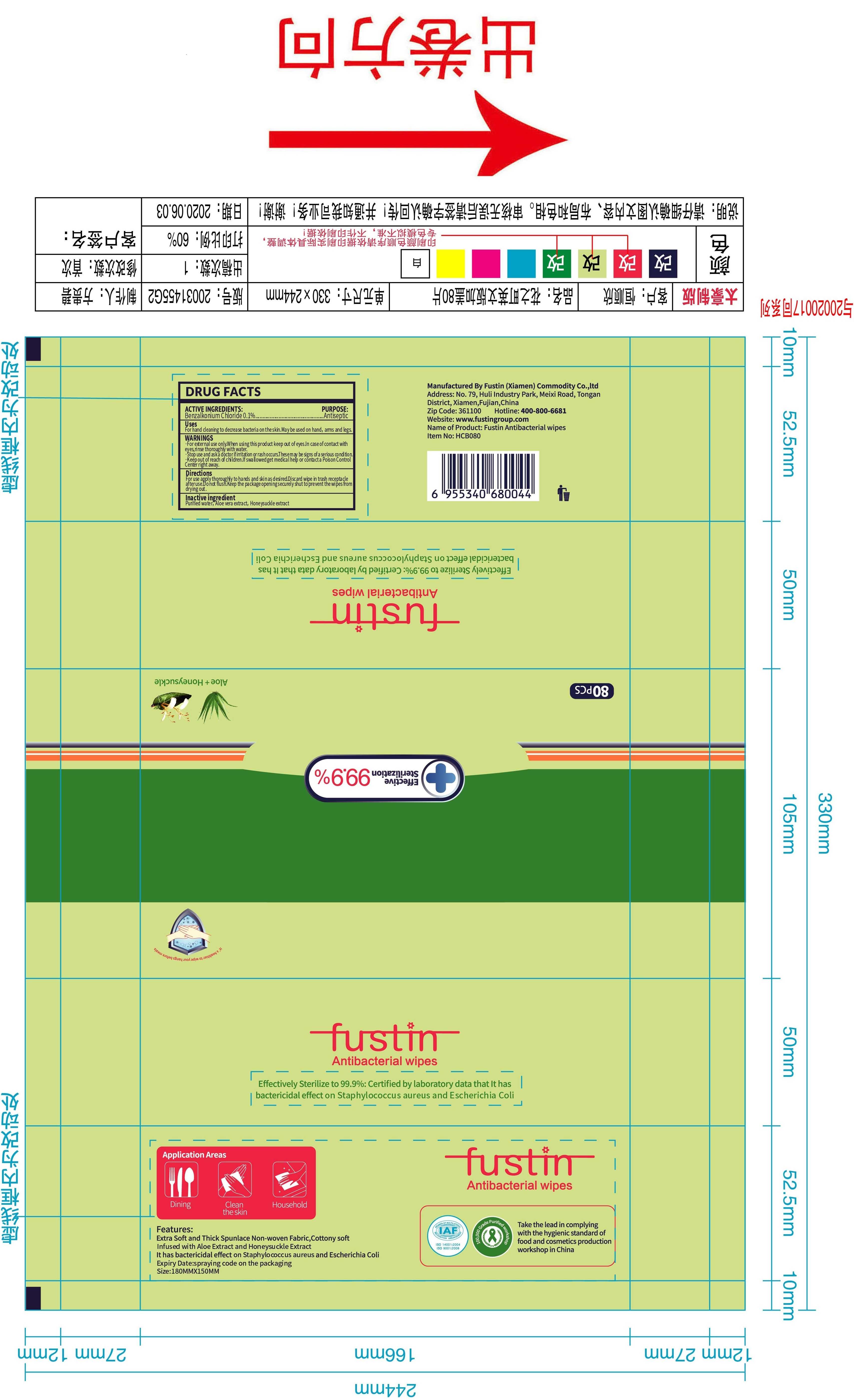 DRUG LABEL: FUSTIN Antibacterial wipes
NDC: 42129-016 | Form: CLOTH
Manufacturer: Fustin(Xiamen) Commodity Co., ltd
Category: otc | Type: HUMAN OTC DRUG LABEL
Date: 20200821

ACTIVE INGREDIENTS: BENZALKONIUM CHLORIDE 0.1 g/100 1
INACTIVE INGREDIENTS: ALOE VERA LEAF; LONICERA CAPRIFOLIUM FLOWER; WATER

42129-016
FUSTIN Antibacterial wipes

Active Ingredient(s)

Benzalkonium Chloride 0.1%

Purpose

Antiseptic

Use

For hand deaning to decrease bacteria on the skin.May be used on hand, arms and legs.

Warnings

·For eJd:ernal use only.When using this prcxl uct keep oot of eyes.In case of contact with eyes,rinse thorough with water.
·Stop use and ask a doctor if irritation or rashoccurs. These may be signs of a serious condition.
·Keep out of reach of crildren.lf swallowed get medical help or contact a Poison Control Center right away.

KEEP OUT OF REACH OF CHILDREN

·Keep out of reach of crildren.lf swallowed get medical help or contact a Poison Control Center right away.

WHEN USING

·For eJd:ernal use only.When using this prcxl uct keep oot of eyes.In case of contact with eyes,rinse thorough with water.
·Stop use and ask a doctor if irritation or rashoccurs. These may be signs of a serious condition.
·Keep out of reach of crildren.lf swallowed get medical help or contact a Poison Control Center right away.

Do not use

/

·Stop use and ask a doctor if irritation or rashoccurs. These may be signs of a serious condition.

Directions

For use apply thoroughly to hands and skinasdesred. Discard wipe in trash receptacle after use. Do not flush. Keep the package opening securely shut to prevent the wipes from drying out.

STORAGE AND HANDLING

/

Inactive ingredients

Purified water, Aloe vera extract, Honeysuckle extract